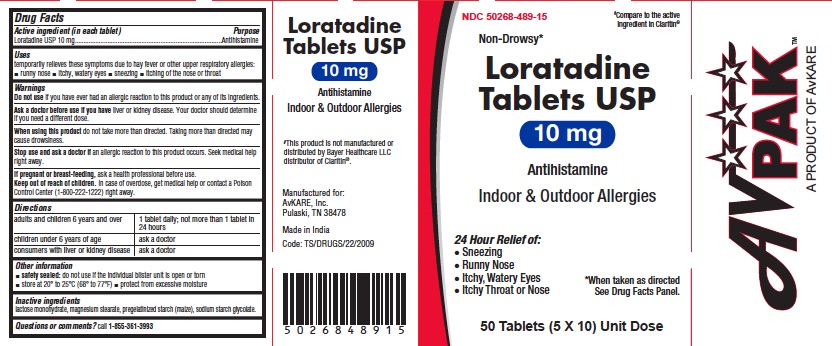 DRUG LABEL: Loratadine
NDC: 50268-489 | Form: TABLET
Manufacturer: AvPAK
Category: otc | Type: HUMAN OTC DRUG LABEL
Date: 20260113

ACTIVE INGREDIENTS: LORATADINE 10 mg/1 1
INACTIVE INGREDIENTS: LACTOSE MONOHYDRATE; MAGNESIUM STEARATE; STARCH, CORN; SODIUM STARCH GLYCOLATE TYPE A POTATO

Loratadine Tablets USP 10 mg

Active ingredient (in each tablet)

Loratadine USP 10 mg

Purpose

Antihistamine

Uses

temporarily relieves these symptoms due to hay fever or other upper respiratory allergies:

- runny nose
- itchy, watery eyes
- sneezing
- itching of the nose or throat

Warnings

Do not use
if you have ever had an allergic reaction to this product or any of its ingredients.

Ask a doctor before use if you have

liver or kidney disease. Your doctor should determine if you need a different dose.

When using this product

do not take more than directed. Taking more than directed may cause drowsiness.

Stop use and ask a doctor if

an allergic reaction to this product occurs. Seek medical help right away.

If pregnant or breast-feeding,

ask a health professional before use.

Keep out of reach of children.

In case of overdose, get medical help or contact a Poison Control Center (1-800-222-1222) right away.

Directions

adults and children 6 years and over | 1 tablet daily; not more than 1 tablet in 24 hours
children under 6 years of age | ask a doctor
consumers with liver or kidney disease | ask a doctor

Other information

- Tamper-evident: do not use if foil seal under cap, printed with “SEALED for YOUR PROTECTION” is missing, open or broken
- store at 20° to 25°C (68° to 77°F)
- protect from excessive moisture

Inactive ingredients

lactose monohydrate, magnesium stearate, pregelatinized starch (maize), sodium starch glycolate.

Questions or comments?

call 1-855-361-3993